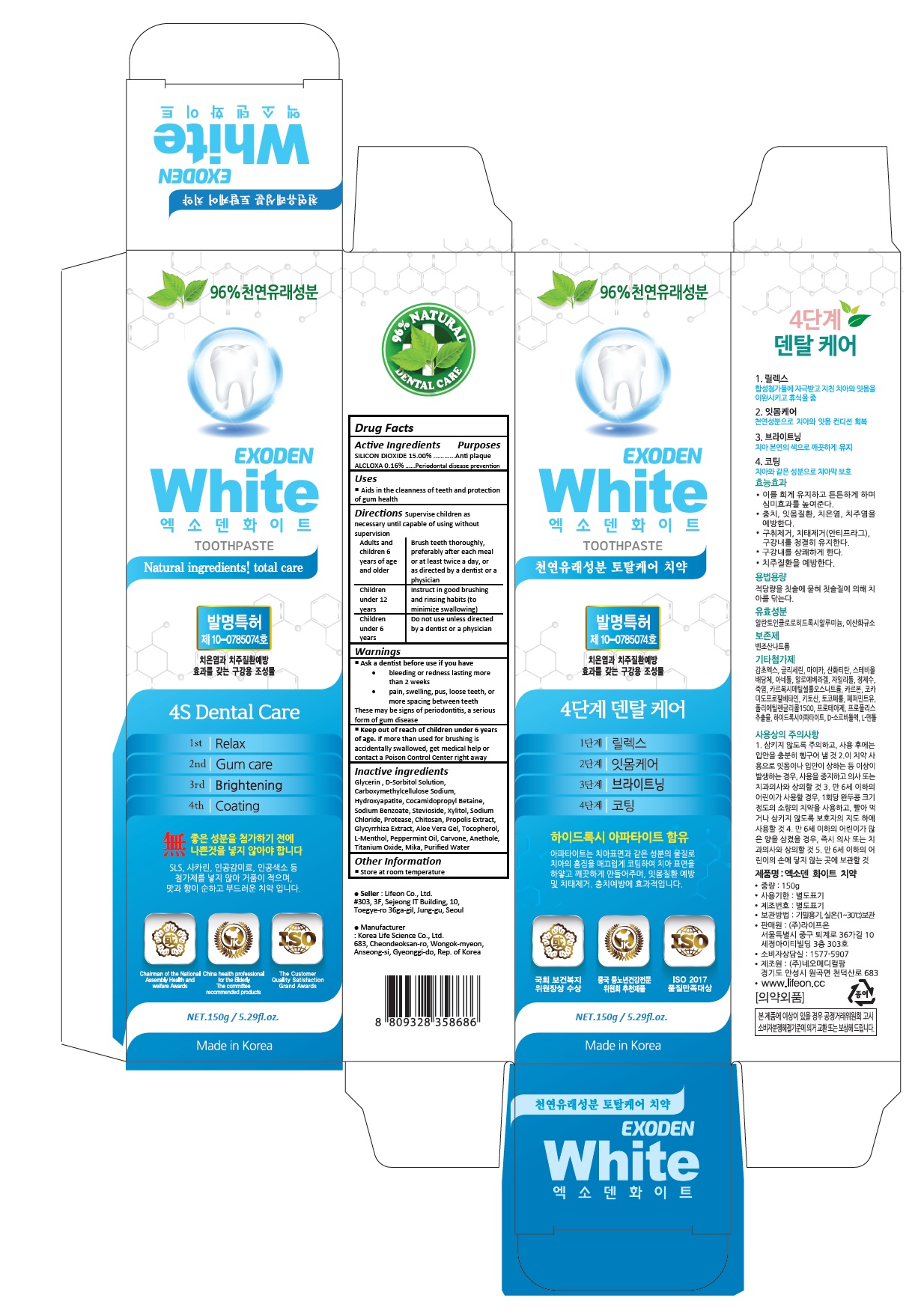 DRUG LABEL: Exoden White
NDC: 70602-008 | Form: PASTE
Manufacturer: LIFEON Corp.
Category: otc | Type: HUMAN OTC DRUG LABEL
Date: 20210312

ACTIVE INGREDIENTS: ALCLOXA 0.16 g/100 g; SILICON DIOXIDE 15 g/100 g
INACTIVE INGREDIENTS: GLYCERIN; SORBITOL SOLUTION; CARBOXYMETHYLCELLULOSE SODIUM, UNSPECIFIED; TRIBASIC CALCIUM PHOSPHATE; COCAMIDOPROPYL BETAINE; SODIUM BENZOATE; GLUCOSYL STEVIOL; XYLITOL; SODIUM CHLORIDE; CHITOSAN LOW MOLECULAR WEIGHT (20-200 MPA.S); PROPOLIS WAX; LICORICE; ALOE VERA LEAF; .ALPHA.-TOCOPHEROL ACETATE; LEVOMENTHOL; PEPPERMINT OIL; CARVONE, (+/-)-; ANETHOLE; TITANIUM DIOXIDE; WATER

70602-008_Exoden White Toothpaste

ACTIVE INGREDIENT

Silicon dioxide 15%

Aluminum Chlorohydroxy Allantoinate 0.16%

PURPOSE

Anti plaque

Periodontal disease prevention

INDICATIONS AND USAGE

Aids in cleanness of teeth and protection of gum health

DOSAGE AND ADMINISTRATION

Supervise children as necessary until capable of using without supervision

Adults and children 6 years of age and older: Brush teeth thoroughly, preferably after each meal or at least twice a day, or as directed by a dentist or a physician

Children under 12 years: Instruct in good brushing and rinsing habits (to minimize swallowing)

Children under 6 years: Do not use unless directed by a dentist or a physician

WARNINGS

Ask a dentist before use if you have
• bleeding or redness lasting more than 2 weeks
• pain, swelling, pus, loose teeth, or more spacing between teeth
These may be signs of periodontitis, a serious form of gum disease

Keep out of reach of children under 6 years of age. If more than used for brushing is accidentally swallowed, get medical help or contact a Poison Control Center right away

INACTIVE INGREDIENT

Glycerin, D-Sorbitol Solution, Carboxymethylcellulose Sodium, Hydroxyapatite, Cocamidopropyl Betaine, Sodium Benzoate, Stevioside, Xylitol, Sodium Chloride, Protease, Chitosan, Propolis Extract, Glycyrrhiza Extract, Aloe Vera Gel, Tocopherol, L-Menthol, Peppermint Oil, Carvone, Anethole, Titanium Oxide, Mika, Purified Water